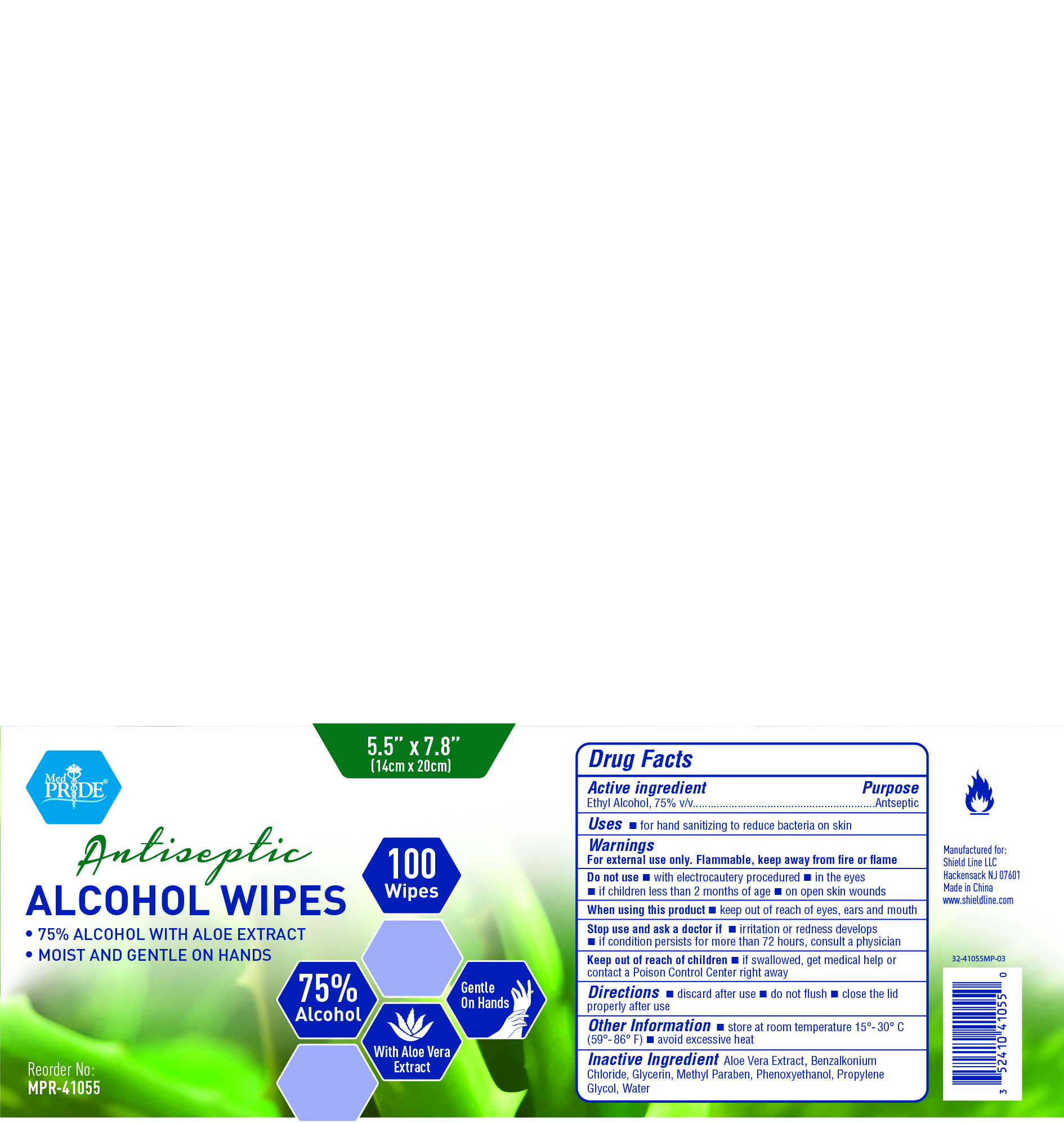 DRUG LABEL: MedPride
NDC: 52410-4105 | Form: CLOTH
Manufacturer: Shield Line LLC
Category: otc | Type: HUMAN OTC DRUG LABEL
Date: 20250815

ACTIVE INGREDIENTS: ALCOHOL 0.75 g/1 1
INACTIVE INGREDIENTS: ALOE VERA LEAF; METHYLPARABEN; PHENOXYETHANOL; BENZALKONIUM CHLORIDE; GLYCERIN; PROPYLENE GLYCOL; WATER

Alcohol Wipes

Active Ingredient

Ethyl Alcohol 75 % v/v

Purpose

Antiseptic

Uses

■ for hand sanitizing to reduce bacteria on skin

Warnings

For external use only
■ flammable, keep away from fire or flame

Do not use

■ with electrocautery procedures ■ in the eyes■ if children less than 2 months of age■ on open skin wounds

When using this product

■ keep out of reach of eyes, ears and mouth

Stop use and ask a doctor if

■if irritation and redness develop ■ if condition persists for more than 72 hours consult a doctor.

Keep out of reach of children.

- If swallowed contact a doctor or Poison Control Center right away.

Directions

■discard after use■do not flush■close the lid properly after use

Other information

■store at room temperature 15° - 30 ° C (59-86 F) ■avoid excessive heat

Inactive Ingredient

Aloe Vera Extract, Benzalkonium Chloride, Glycerin, Methyl Paraben, Phenoxyethanol, Propylene Glycol, water